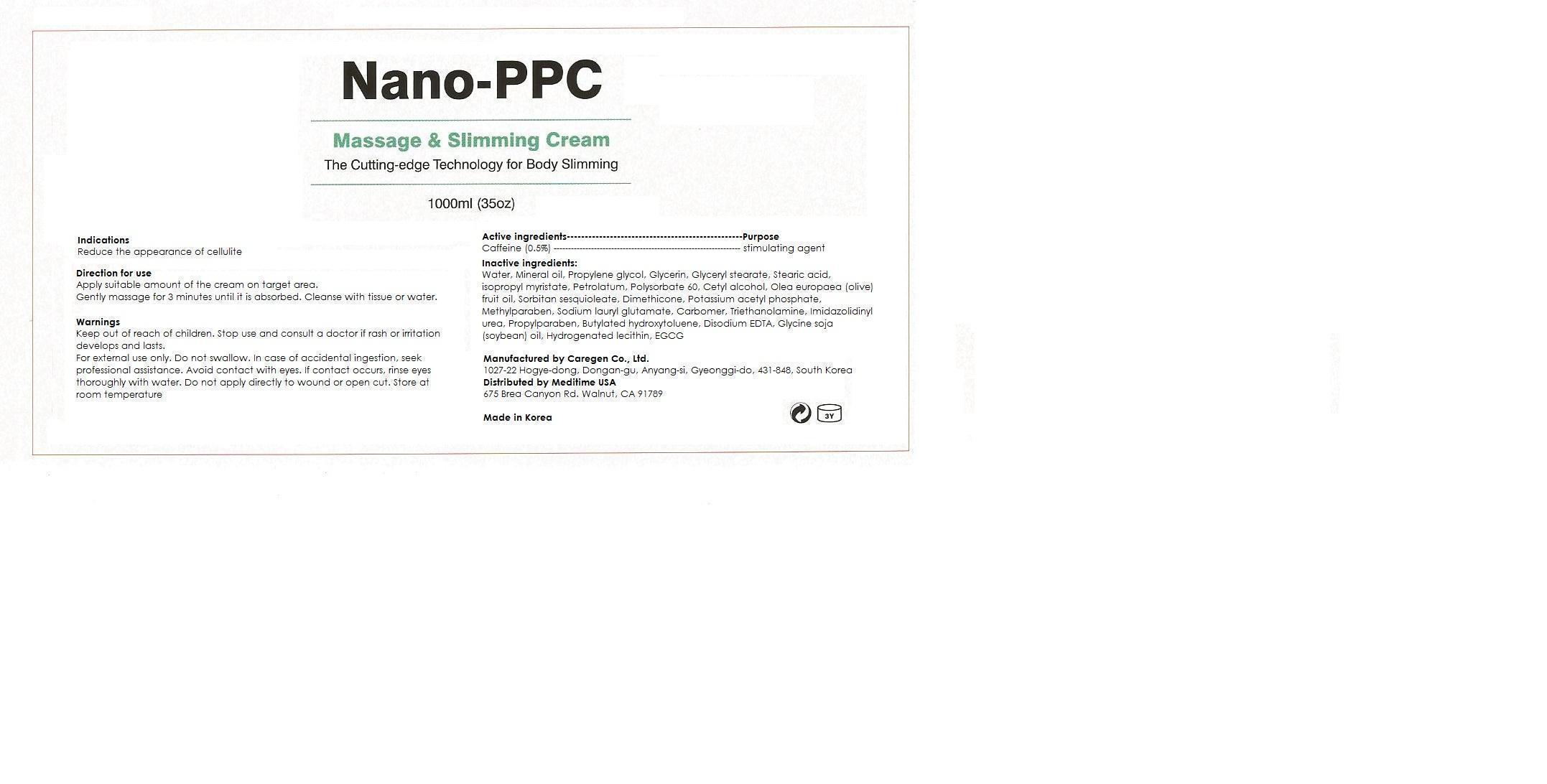 DRUG LABEL: NANO PPC
NDC: 60709-100 | Form: CREAM
Manufacturer: YBK Investment, INC
Category: otc | Type: HUMAN OTC DRUG LABEL
Date: 20131004

ACTIVE INGREDIENTS: CAFFEINE 5.0 mg/1000 mL
INACTIVE INGREDIENTS: water; MINERAL OIL; PROPYLENE GLYCOL; GLYCERIN; GLYCERYL STEARATE SE; STEARIC ACID; ISOPROPYL MYRISTATE; PETROLATUM; POLYSORBATE 60; OLEA EUROPAEA FRUIT VOLATILE OIL; SORBITAN SESQUIOLEATE; DIMETHICONE; POTASSIUM CETYL PHOSPHATE; METHYLPARABEN; SODIUM LAUROYL GLUTAMATE; CARBOMER 1342; PROPYLPARABEN; BUTYLATED HYDROXYTOLUENE; SOYBEAN OIL; HYDROGENATED SOYBEAN LECITHIN; EPIGALLOCATECHIN GALLATE; YELLOW WAX; LEVOCARNITINE

NANO-PPC

NANO-PPC massage and slimming cream

Active ingredients: Caffeine (0.5%)

Keep out of reach of children

INDICATIONS AND USAGE

Direction for use

Apply suitable amount of the cream on target area.

Gently massage for 3 minutes until it is absorbed. Cleanse with tissue or water.

WARNINGS

Cautions

For external use only, not to be swallowed. In case of accidental ingestion, seek professional assistance. Avoid contact with eyes. If contact occurs, rinse eyes thoroughly with water. Do not apply directly to wound or open cut. Store at room temperature

PURPOSE

Reduce the appearance of cellulite

Inactive ingredients:

Water, Mineral oil, Propylene glycol, Glycerin, Glyceryl stearate, Stearic acid, isopropyl myristate, Petrolatum, Polysorbate 60, Cetyl alcohol, Olea europaea (olive) fruit oil, Sorbitan sesquioleate, Dimethicone, Potassium acetyl phosphate, Methylparaben, Sodium lauryl glutamate, Carbomer, Triethanolamine, Imidazolidinyl urea, Propylparaben, Butylated hydroxytoluene, Disodium EDTA, Glycine soja (soybean) oil, Hydrogenated lecithin, Carnitine

DOSAGE AND ADMINISTRATION

massage skin

reduce the appearance of cellulite

Stop use and consult a doctor if rash or irritation develops and lasts.

WARNINGS AND PRECAUTIONS

Cautions

For external use only, not to be swallowed. In case of accidental ingestion, seek professional assistance. Avoid contact with eyes. If contact occurs, rinse eyes thoroughly with water. Do not apply directly to wound or open cut. Store at room temperature